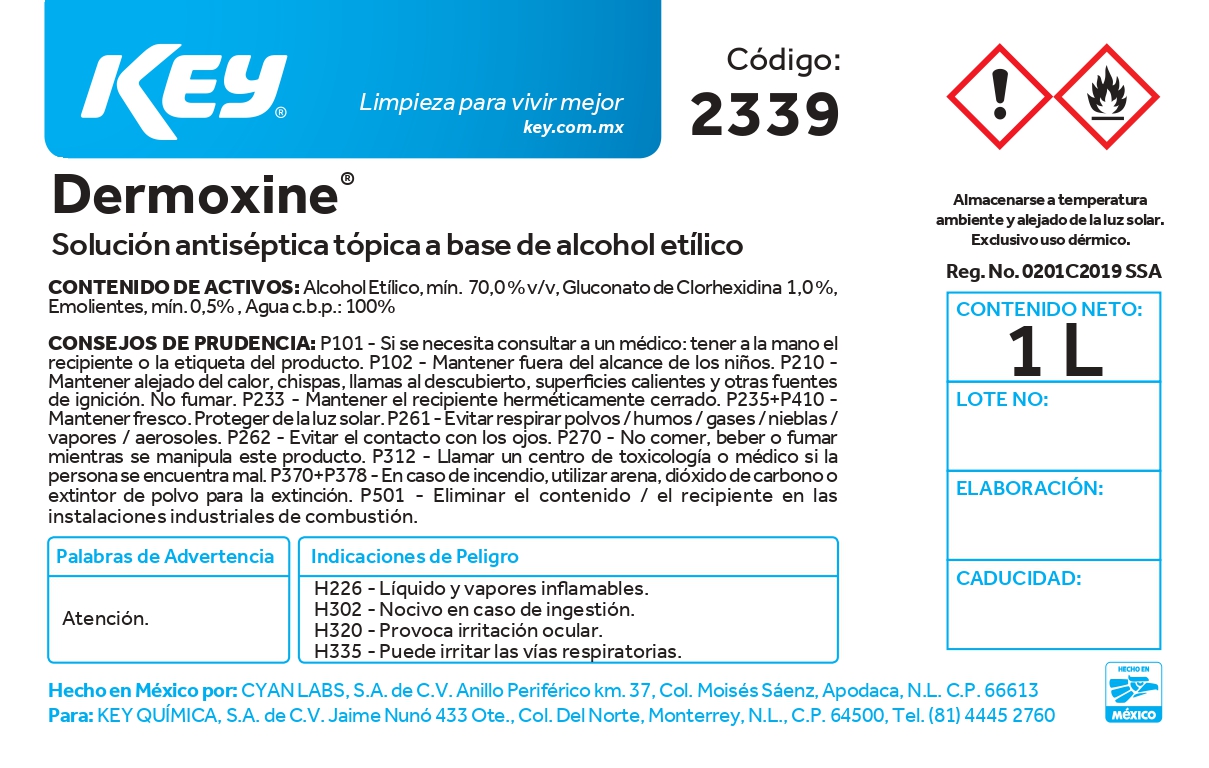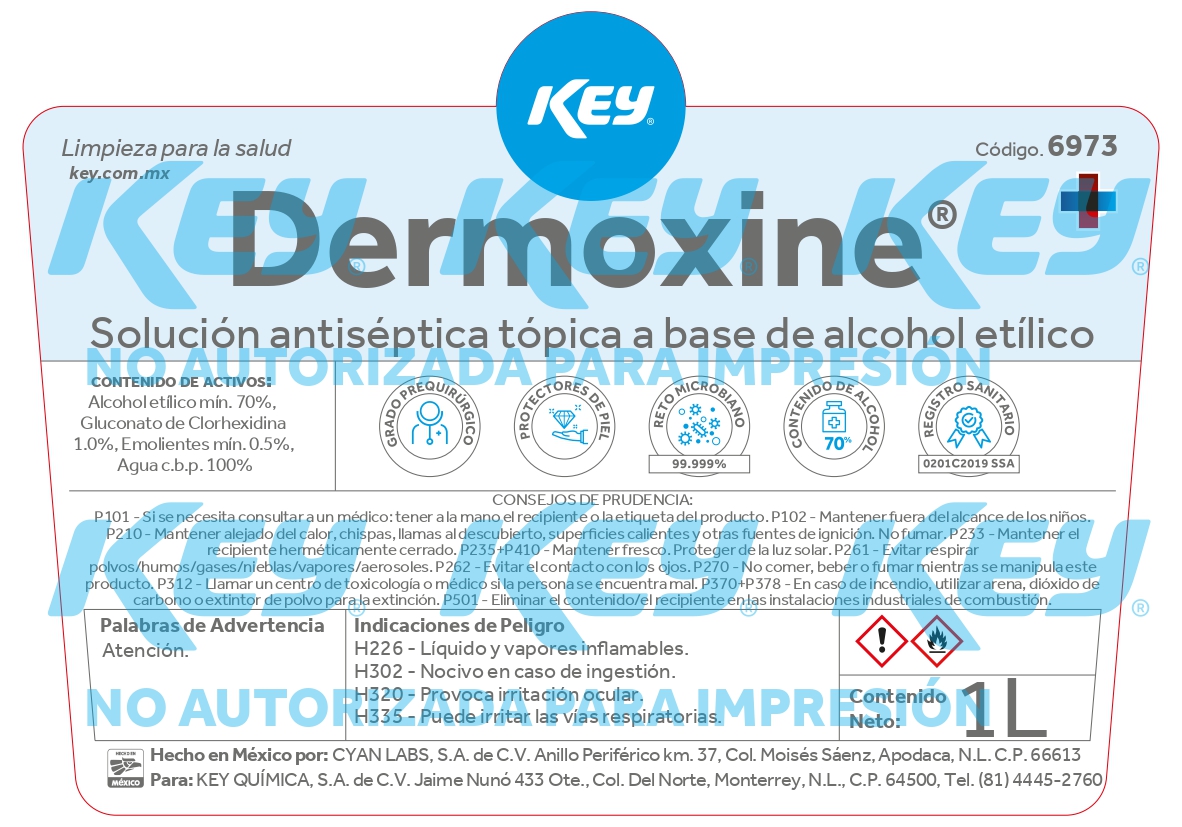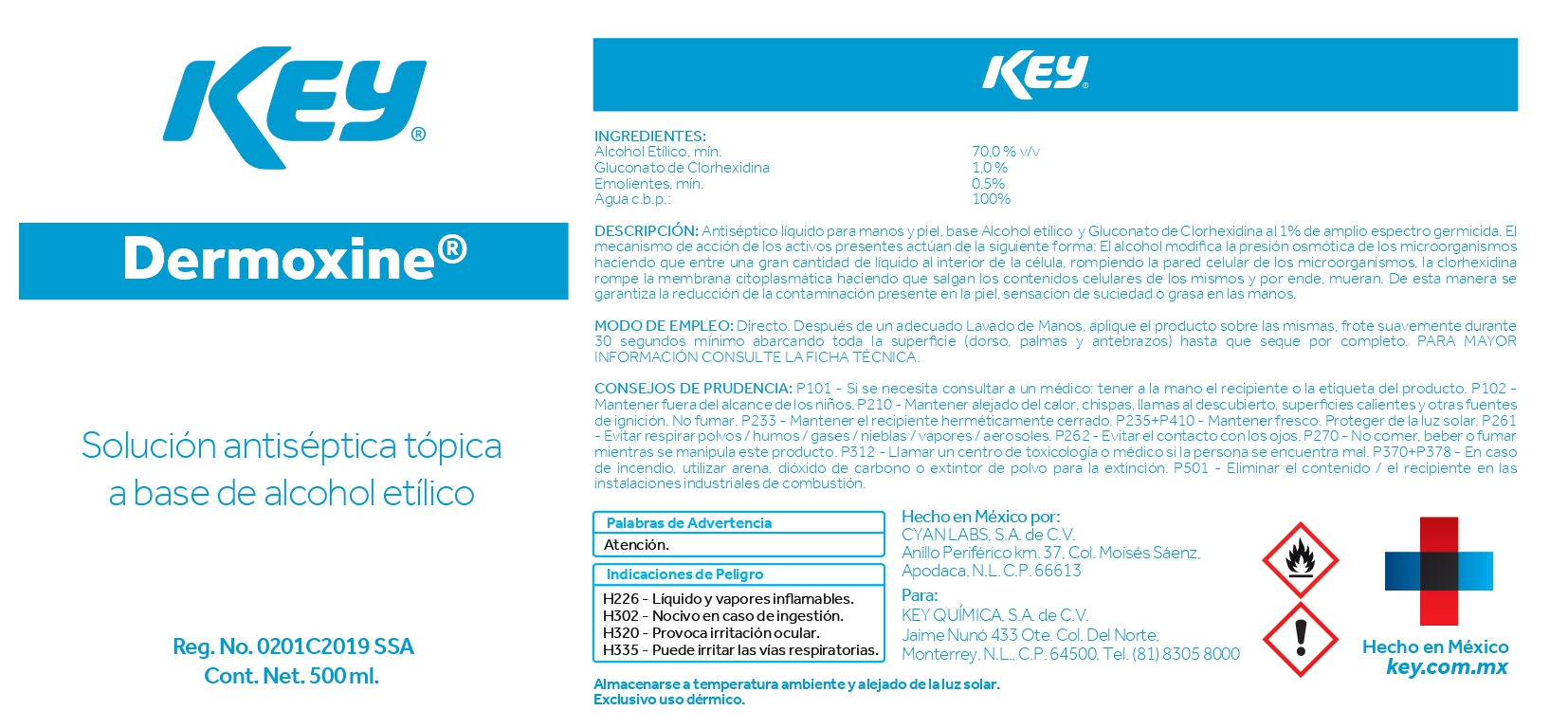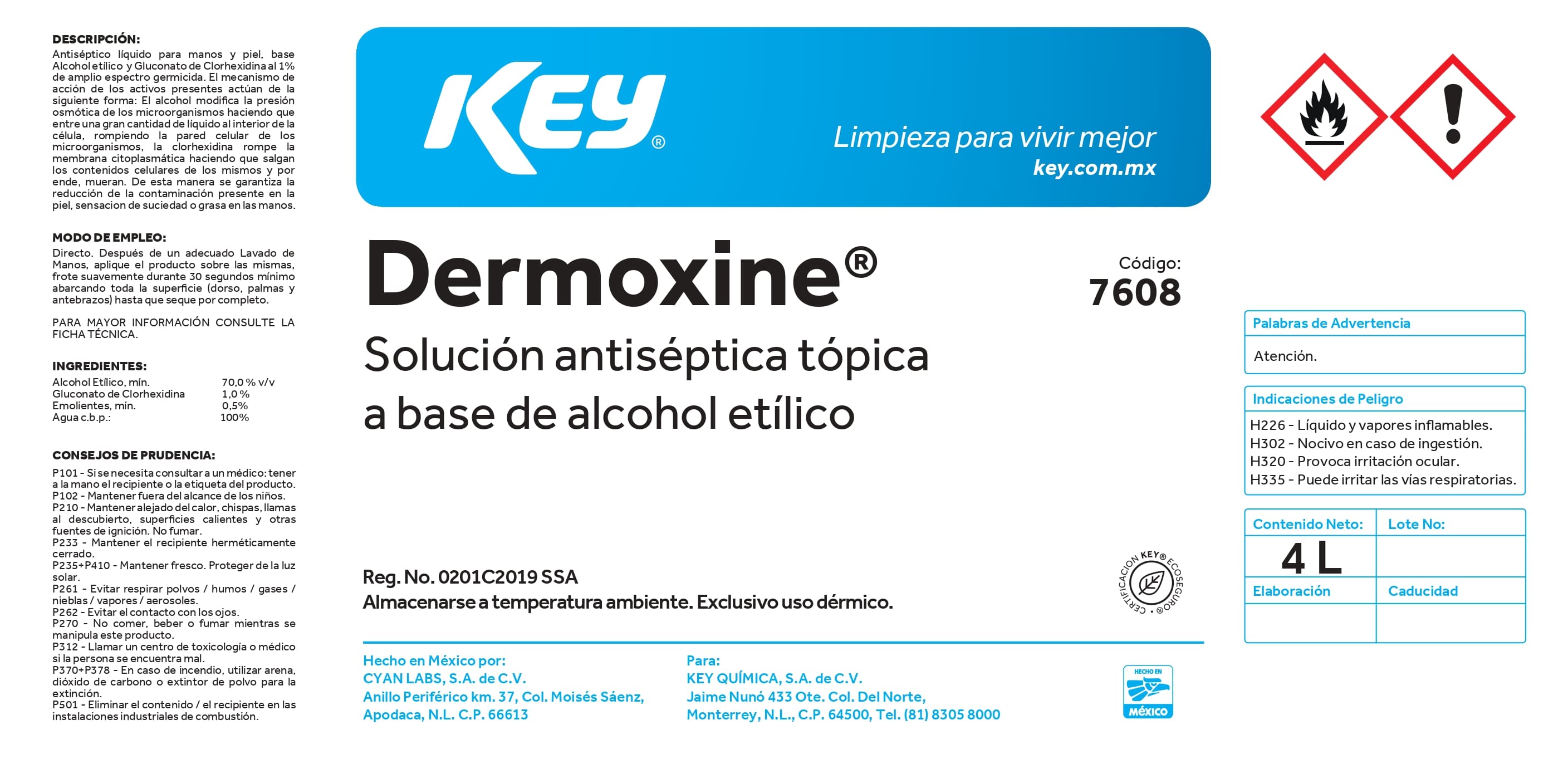 DRUG LABEL: Solucion Antiseptica Dermoxine
NDC: 58345-106 | Form: LIQUID
Manufacturer: Key Química S.A. de C.V.
Category: otc | Type: HUMAN OTC DRUG LABEL
Date: 20240918

ACTIVE INGREDIENTS: CHLORHEXIDINE GLUCONATE 0.97 g/100 mL; ALCOHOL 70 mL/100 mL
INACTIVE INGREDIENTS: WATER; .ALPHA.-TOCOPHEROL; GLYCERIN

58345-106

Contenido de activos

Alcohol Etílico, min 70.0 % v/v

Gluconato de Clorhexidina 1.0 %

Emolientes, min 0.5 %

Agua c.b.p. 100 %

Descripción

Antiséptico líquido para manos y piel, base Alcohol Etílico y Gluconato de Clorhexidina al 1 % de amplio espectro germicida. El mecanismo de acción de los activos presentes actúan de la siguiente forma: el alcohol modifica la presión osmótica de los microorganismos haciendo que entre una gran cantidad de líquido al interior de la célula, rompiendo la pared celular de los microorganismos. La Clorhexidina rompe la membrana citoplasmática haciendo que salgan los contenidos celulares de los mismos y por ende, mueran. De esta manera se garantiza la reducción de la contaminación presente en la piel, sensacion de suciedad o grasa en las manos.

Modo de empleo

Directo. Después de un adecuado lavado de manos, aplique el producto sobre las mismas, frote suavemente durante 30 segundos mínimo abarcando toda la superficie (dorso, palmas y antebrazos) hasta que seque por completo. PARA MAYOR INFORMACIÓN CONSULTE LA FICHA TÉCNICA.

Consejos de prudencia

P101 - Si se necesita consultar a un médico: tener a la mano el recipiente o la etiqueta del producto. P102 - Mantener fuera del alcance de los niños. P210 - Mantejer alejado del calor, chispas, llamas al descubierto, superficies calientes y otras fuentes de ignición. No fumar. P233 - Mantener el recipiente herméticamente cerrado. P235+P410 - Mantener fresco. Proteger de la luz solar. P261 - Evitar respirar polvos, humos, gases, nieblas, vapores y aerosoles. P262 - Evitar contacto con los ojos. P270 - No comer, beber o fumar mientras se manipula este producto. P312 - Llamar a un centro de toxicología o médico si la persona se encuentra mal. P370+378 - En caso de incendio, utilizar arena, dióxido de carbono o extintor de polvo para la extinción. P501 - Eliminar el contenido / el recipiente en las instalaciones industriales de combustión.

Palabras de advertencia

Atención

Indicaciones de peligro

H226 - Líquido y vapores inflamables.

H302 - Nocivo en caso de ingestión.

H320 - Provoca irritación ocular.

H335 - Puede irritar las vías respiratorias.

Active ingredients

Alcohol 70 % v/v

Gluconato de Clorhexidina 1 %

Purpose

Antiseptic

Do not use this product in or near the eyes.

Stop use if irritation or redness develop. If contidions persist for more than 72 hours, consult a doctor.

Keep out of reach of children. If swallowed, seek inmediate medical attention or call a poison center.

Inactive ingredients

Water (aqua), moisturizers.